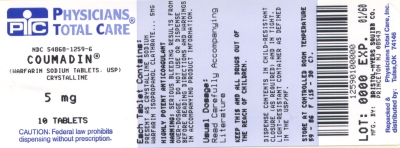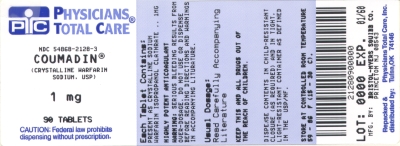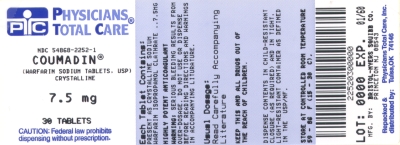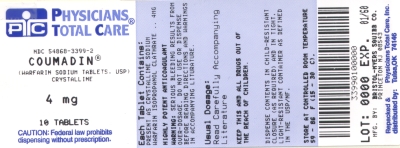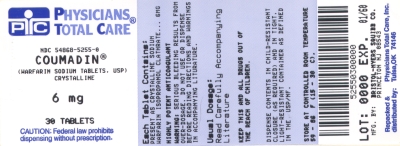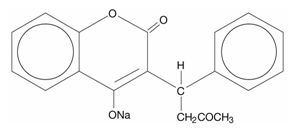 DRUG LABEL: COUMADIN
NDC: 54868-2128 | Form: TABLET
Manufacturer: Physicians Total Care, Inc.
Category: prescription | Type: HUMAN PRESCRIPTION DRUG LABEL
Date: 20121115

ACTIVE INGREDIENTS: warfarin sodium 1 mg/1 1
INACTIVE INGREDIENTS: lactose; starch, tapioca; magnesium stearate; D&C Red No. 6; barium sulfate

HIGHLIGHTS OF PRESCRIBING INFORMATION

These highlights do not include all the information needed to use COUMADIN safely and effectively. See full prescribing information for COUMADIN.
COUMADIN (warfarin sodium) tablets, for oral use
COUMADIN (warfarin sodium) for injection, for intravenous use
Initial U.S. Approval: 1954

WARNING: BLEEDING RISK

See full prescribing information for complete boxed warning.

- COUMADIN can cause major or fatal bleeding. (5.1)
- Perform regular monitoring of INR in all treated patients. (2.1)
- Drugs, dietary changes, and other factors affect INR levels achieved with COUMADIN therapy. (7)
- Instruct patients about prevention measures to minimize risk of bleeding and to report signs and symptoms of bleeding. (17)

RECENT MAJOR CHANGES

Contraindications (4) 10/2011

Warnings and Precautions, Use in Pregnant Women with Mechanical Heart Valves (5.5) 10/2011

1 INDICATIONS AND USAGE

COUMADIN is a vitamin K antagonist indicated for:

- Prophylaxis and treatment of venous thrombosis and its extension, pulmonary embolism (1)
- Prophylaxis and treatment of thromboembolic complications associated with atrial fibrillation and/or cardiac valve replacement (1)
- Reduction in the risk of death, recurrent myocardial infarction, and thromboembolic events such as stroke or systemic embolization after myocardial infarction (1)

Limitation of Use

COUMADIN has no direct effect on an established thrombus, nor does it reverse ischemic tissue damage. (1)

2 DOSAGE AND ADMINISTRATION

- Individualize dosing regimen for each patient, and adjust based on INR response. (2.1, 2.2)
- Knowledge of genotype can inform initial dose selection. (2.3)
- Monitoring: Obtain daily INR determinations upon initiation until stable in the therapeutic range. Obtain subsequent INR determinations every 1 to 4 weeks. (2.4)
- Review conversion instructions from other anticoagulants. (2.8)

3 DOSAGE FORMS AND STRENGTHS

- Scored tablets: 1, 2, 2-1/2, 3, 4, 5, 6, 7-1/2, or 10 mg (3)
- For injection: Vial containing 5 mg lyophilized powder (3)

4 CONTRAINDICATIONS

- Pregnancy, except in women with mechanical heart valves (4)
- Hemorrhagic tendencies or blood dyscrasias (4)
- Recent or contemplated surgery of the central nervous system (CNS) or eye, or traumatic surgery resulting in large open surfaces (4, 5.7)
- Bleeding tendencies associated with certain conditions (4)
- Threatened abortion, eclampsia, and preeclampsia (4)
- Unsupervised patients with potential high levels of non-compliance (4)
- Spinal puncture and other diagnostic or therapeutic procedures with potential for uncontrollable bleeding (4)
- Hypersensitivity to warfarin or any component of the product (4)
- Major regional or lumbar block anesthesia (4)
- Malignant hypertension (4)

5 WARNINGS AND PRECAUTIONS

- Tissue necrosis: Necrosis or gangrene of skin or other tissues can occur, with severe cases requiring debridement or amputation. Discontinue COUMADIN and consider alternative anticoagulants if necessary. (5.2)
- Systemic atheroemboli and cholesterol microemboli: Some cases have progressed to necrosis or death. Discontinue COUMADIN if such emboli occur. (5.3)
- Heparin-induced thrombocytopenia (HIT): Initial therapy with COUMADIN in HIT has resulted in cases of amputation and death. COUMADIN may be considered after platelet count has normalized. (5.4)
- Pregnant women with mechanical heart valves: COUMADIN may cause fetal harm; however, the benefits may outweigh the risks. (5.5)

6 ADVERSE REACTIONS

Most common adverse reactions to COUMADIN are fatal and nonfatal hemorrhage from any tissue or organ. (6)

To report SUSPECTED ADVERSE REACTIONS, contact Bristol-Myers Squibb at 1-800-721-5072 or FDA at 1-800-FDA-1088 or www.fda.gov/medwatch.

7 DRUG INTERACTIONS

- Consult labeling of all concurrently used drugs for complete information about interactions with COUMADIN or increased risks for bleeding. (7)
- Inhibitors and inducers of CYP2C9, 1A2, or 3A4: May alter warfarin exposure. Monitor INR closely when any such drug is used with COUMADIN. (7.1)
- Drugs that increase bleeding risk: Closely monitor patients receiving any such drug (e.g., other anticoagulants, antiplatelet agents, nonsteroidal anti-inflammatory drugs, serotonin reuptake inhibitors). (7.2)
- Antibiotics and antifungals: Closely monitor INR when initiating or stopping an antibiotic or antifungal course of therapy. (7.3)
- Botanical (herbal) products: Some may influence patient response to COUMADIN necessitating close INR monitoring. (7.4)

8 USE IN SPECIFIC POPULATIONS

- Nursing mothers: Use with caution in a nursing woman. Monitor breast-feeding infants for bruising or bleeding. (8.3)

FULL PRESCRIBING INFORMATION

WARNING: BLEEDING RISK

- COUMADIN can cause major or fatal bleeding [see Warnings and Precautions (5.1)].
- Perform regular monitoring of INR in all treated patients [see Dosage and Administration (2.1)].
- Drugs, dietary changes, and other factors affect INR levels achieved with COUMADIN therapy [see Drug Interactions (7)].
- Instruct patients about prevention measures to minimize risk of bleeding and to report signs and symptoms of bleeding [see Patient Counseling Information (17)].

1 INDICATIONS AND USAGE

COUMADIN® is indicated for:

- Prophylaxis and treatment of venous thrombosis and its extension, pulmonary embolism (PE).
- Prophylaxis and treatment of thromboembolic complications associated with atrial fibrillation (AF) and/or cardiac valve replacement.
- Reduction in the risk of death, recurrent myocardial infarction (MI), and thromboembolic events such as stroke or systemic embolization after myocardial infarction.

Limitations of Use

COUMADIN has no direct effect on an established thrombus, nor does it reverse ischemic tissue damage. Once a thrombus has occurred, however, the goals of anticoagulant treatment are to prevent further extension of the formed clot and to prevent secondary thromboembolic complications that may result in serious and possibly fatal sequelae.

2 DOSAGE AND ADMINISTRATION

2.1 Individualized Dosing

The dosage and administration of COUMADIN must be individualized for each patient according to the patient’s INR response to the drug. Adjust the dose based on the patient’s INR and the condition being treated. Consult the latest evidence-based clinical practice guidelines from the American College of Chest Physicians (ACCP) to assist in the determination of the duration and intensity of anticoagulation with COUMADIN [see References (15)].

2.2 Recommended Target INR Ranges and Durations for Individual Indications

An INR of greater than 4.0 appears to provide no additional therapeutic benefit in most patients and is associated with a higher risk of bleeding.

Venous Thromboembolism (including deep venous thrombosis [DVT] and PE)

Adjust the warfarin dose to maintain a target INR of 2.5 (INR range, 2.0-3.0) for all treatment durations. The duration of treatment is based on the indication as follows:

- For patients with a DVT or PE secondary to a transient (reversible) risk factor, treatment with warfarin for 3 months is recommended.
- For patients with an unprovoked DVT or PE, treatment with warfarin is recommended for at least 3 months. After 3 months of therapy, evaluate the risk-benefit ratio of long-term treatment for the individual patient.
- For patients with two episodes of unprovoked DVT or PE, long-term treatment with warfarin is recommended. For a patient receiving long-term anticoagulant treatment, periodically reassess the risk-benefit ratio of continuing such treatment in the individual patient.

Atrial Fibrillation

In patients with non-valvular AF, anticoagulate with warfarin to target INR of 2.5 (range, 2.0-3.0).

- In patients with non-valvular AF that is persistent or paroxysmal and at high risk of stroke (i.e., having any of the following features: prior ischemic stroke, transient ischemic attack, or systemic embolism, or 2 of the following risk factors: age greater than 75 years, moderately or severely impaired left ventricular systolic function and/or heart failure, history of hypertension, or diabetes mellitus), long-term anticoagulation with warfarin is recommended.
- In patients with non-valvular AF that is persistent or paroxysmal and at an intermediate risk of ischemic stroke (i.e., having 1 of the following risk factors: age greater than 75 years, moderately or severely impaired left ventricular systolic function and/or heart failure, history of hypertension, or diabetes mellitus), long-term anticoagulation with warfarin is recommended.
- For patients with AF and mitral stenosis, long-term anticoagulation with warfarin is recommended.
- For patients with AF and prosthetic heart valves, long-term anticoagulation with warfarin is recommended; the target INR may be increased and aspirin added depending on valve type and position, and on patient factors.

Mechanical and Bioprosthetic Heart Valves

- For patients with a bileaflet mechanical valve or a Medtronic Hall (Minneapolis, MN) tilting disk valve in the aortic position who are in sinus rhythm and without left atrial enlargement, therapy with warfarin to a target INR of 2.5 (range, 2.0-3.0) is recommended.
- For patients with tilting disk valves and bileaflet mechanical valves in the mitral position, therapy with warfarin to a target INR of 3.0 (range, 2.5-3.5) is recommended.
- For patients with caged ball or caged disk valves, therapy with warfarin to a target INR of 3.0 (range, 2.5-3.5) is recommended.
- For patients with a bioprosthetic valve in the mitral position, therapy with warfarin to a target INR of 2.5 (range, 2.0-3.0) for the first 3 months after valve insertion is recommended. If additional risk factors for thromboembolism are present (AF, previous thromboembolism, left ventricular dysfunction), a target INR of 2.5 (range, 2.0-3.0) is recommended.

Post-Myocardial Infarction

- For high-risk patients with MI (e.g., those with a large anterior MI, those with significant heart failure, those with intracardiac thrombus visible on transthoracic echocardiography, those with AF, and those with a history of a thromboembolic event), therapy with combined moderate-intensity (INR, 2.0-3.0) warfarin plus low-dose aspirin (≤100 mg/day) for at least 3 months after the MI is recommended.

Recurrent Systemic Embolism and Other Indications

Oral anticoagulation therapy with warfarin has not been fully evaluated by clinical trials in patients with valvular disease associated with AF, patients with mitral stenosis, and patients with recurrent systemic embolism of unknown etiology. However, a moderate dose regimen (INR 2.0-3.0) may be used for these patients.

2.3 Initial and Maintenance Dosing

The appropriate initial dosing of COUMADIN varies widely for different patients. Not all factors responsible for warfarin dose variability are known, and the initial dose is influenced by:

- Clinical factors including age, race, body weight, sex, concomitant medications, and comorbidities
- Genetic factors (CYP2C9 and VKORC1 genotypes) [see Clinical Pharmacology (12.5)]

Select the initial dose based on the expected maintenance dose, taking into account the above factors. Modify this dose based on consideration of patient-specific clinical factors. Consider lower initial and maintenance doses for elderly and/or debilitated patients and in Asian patients [see Use in Specific Populations (8.5) and Clinical Pharmacology (12.3)]. Routine use of loading doses is not recommended as this practice may increase hemorrhagic and other complications and does not offer more rapid protection against clot formation.

Individualize the duration of therapy for each patient. In general, anticoagulant therapy should be continued until the danger of thrombosis and embolism has passed [see Dosage and Administration (2.2)].

Dosing Recommendations without Consideration of Genotype

If the patient’s CYP2C9 and VKORC1 genotypes are not known, the initial dose of COUMADIN is usually 2 to 5 mg once daily. Determine each patient’s dosing needs by close monitoring of the INR response and consideration of the indication being treated. Typical maintenance doses are 2 to 10 mg once daily.

Dosing Recommendations with Consideration of Genotype

Table 1 displays three ranges of expected maintenance COUMADIN doses observed in subgroups of patients having different combinations of CYP2C9 and VKORC1 gene variants [see Clinical Pharmacology (12.5)]. If the patient’s CYP2C9 and/or VKORC1 genotype are known, consider these ranges in choosing the initial dose. Patients with CYP2C9 *1/*3, *2/*2, *2/*3, and *3/*3 may require more prolonged time (>2 to 4 weeks) to achieve maximum INR effect for a given dosage regimen than patients without these CYP variants.

Table 1: Three Ranges of Expected Maintenance COUMADIN Daily Doses Based on CYP2C9 and VKORC1 Genotypes†
VKORC1 | CYP2C9
VKORC1 | *1/*1 | *1/*2 | *1/*3 | *2/*2 | *2/*3 | *3/*3
GG | 5-7 mg | 5-7 mg | 3-4 mg | 3-4 mg | 3-4 mg | 0.5-2 mg
AG | 5-7 mg | 3-4 mg | 3-4 mg | 3-4 mg | 0.5-2 mg | 0.5-2 mg
AA | 3-4 mg | 3-4 mg | 0.5-2 mg | 0.5-2 mg | 0.5-2 mg | 0.5-2 mg
†Ranges are derived from multiple published clinical studies. VKORC1 –1639G>A (rs9923231) variant is used in this table. Other co-inherited VKORC1 variants may also be important determinants of warfarin dose.

2.4 Monitoring to Achieve Optimal Anticoagulation

COUMADIN is a narrow therapeutic range (index) drug, and its action may be affected by factors such as other drugs and dietary vitamin K. Therefore, anticoagulation must be carefully monitored during COUMADIN therapy. Determine the INR daily after the administration of the initial dose until INR results stabilize in the therapeutic range. After stabilization, maintain dosing within the therapeutic range by performing periodic INRs. The frequency of performing INR should be based on the clinical situation but generally acceptable intervals for INR determinations are 1 to 4 weeks. Perform additional INR tests when other warfarin products are interchanged with COUMADIN, as well as whenever other medications are initiated, discontinued, or taken irregularly. Heparin, a common concomitant drug, increases the INR [see Dosage and Administration (2.8) and Drug Interactions (7)].

Determinations of whole blood clotting and bleeding times are not effective measures for monitoring of COUMADIN therapy.

2.5 Missed Dose

The anticoagulant effect of COUMADIN persists beyond 24 hours. If a patient misses a dose of COUMADIN at the intended time of day, the patient should take the dose as soon as possible on the same day. The patient should not double the dose the next day to make up for a missed dose.

2.6 Intravenous Route of Administration

The intravenous dose of COUMADIN is the same as the oral dose. After reconstitution, COUMADIN for injection should be administered as a slow bolus injection into a peripheral vein over 1 to 2 minutes. COUMADIN for injection is not recommended for intramuscular administration.

Reconstitute the vial with 2.7 mL of Sterile Water for Injection. The resulting yield is 2.5 mL of a 2 mg per mL solution (5 mg total). Parenteral drug products should be inspected visually for particulate matter and discoloration prior to administration. Do not use if particulate matter or discoloration is noted.

After reconstitution, COUMADIN for injection is stable for 4 hours at room temperature. It does not contain any antimicrobial preservative and, thus, care must be taken to assure the sterility of the prepared solution. The vial is for single use only, and any unused solution should be discarded.

2.7 Treatment During Dentistry and Surgery

Some dental or surgical procedures may necessitate the interruption or change in the dose of COUMADIN therapy. Consider the benefits and risks when discontinuing COUMADIN even for a short period of time. Determine the INR immediately prior to any dental or surgical procedure. In patients undergoing minimally invasive procedures who must be anticoagulated prior to, during, or immediately following these procedures, adjusting the dosage of COUMADIN to maintain the INR at the low end of the therapeutic range may safely allow for continued anticoagulation.

2.8 Conversion From Other Anticoagulants

Heparin

Since the full anticoagulant effect of COUMADIN is not achieved for several days, heparin is preferred for initial rapid anticoagulation. During initial therapy with COUMADIN, the interference with heparin anticoagulation is of minimal clinical significance. Conversion to COUMADIN may begin concomitantly with heparin therapy or may be delayed 3 to 6 days. To ensure therapeutic anticoagulation, continue full dose heparin therapy and overlap COUMADIN therapy with heparin for 4 to 5 days and until COUMADIN has produced the desired therapeutic response as determined by INR, at which point heparin may be discontinued.

As heparin may affect the INR, patients receiving both heparin and COUMADIN should have INR monitoring at least:

- 5 hours after the last intravenous bolus dose of heparin, or
- 4 hours after cessation of a continuous intravenous infusion of heparin, or
- 24 hours after the last subcutaneous heparin injection.

COUMADIN may increase the activated partial thromboplastin time (aPTT) test, even in the absence of heparin. A severe elevation (>50 seconds) in aPTT with an INR in the desired range has been identified as an indication of increased risk of postoperative hemorrhage.

Other Anticoagulants

Consult the labeling of other anticoagulants for instructions on conversion to COUMADIN.

3 DOSAGE FORMS AND STRENGTHS

COUMADIN tablets are single scored with one face imprinted numerically with 1, 2, 2-1/2, 3, 4, 5, 6, 7-1/2, or 10 superimposed and inscribed with “COUMADIN” and with the opposite face plain.

COUMADIN tablets are supplied in the following strengths:

COUMADIN Tablets
Strength | Color
1 mg | pink
2 mg | lavender
2-1/2 mg | green
3 mg | tan
4 mg | blue
5 mg | peach
6 mg | teal
7-1/2 mg | yellow
10 mg | white (dye-free)

COUMADIN for injection is available in a vial containing 5 mg of lyophilized powder.

4 CONTRAINDICATIONS

- Pregnancy

COUMADIN is contraindicated in women who are pregnant except in pregnant women with mechanical heart valves, who are at high risk of thromboembolism [see Warnings and Precautions (5.5) and Use in Specific Populations (8.1)]. COUMADIN can cause fetal harm when administered to a pregnant woman. COUMADIN exposure during pregnancy causes a recognized pattern of major congenital malformations (warfarin embryopathy and fetotoxicity), fatal fetal hemorrhage, and an increased risk of spontaneous abortion and fetal mortality. If COUMADIN is used during pregnancy or if the patient becomes pregnant while taking this drug, the patient should be apprised of the potential hazard to a fetus [see Warnings and Precautions (5.6) and Use in Specific Populations (8.1)].

- Hemorrhagic tendencies or blood dyscrasias
- Recent or contemplated surgery of the central nervous system or eye, or traumatic surgery resulting in large open surfaces [see Warnings and Precautions (5.7)]
- Bleeding tendencies associated with:
  - Active ulceration or overt bleeding of the gastrointestinal, genitourinary, or respiratory tract
  - Central nervous system hemorrhage
  - Cerebral aneurysms, dissecting aorta
  - Pericarditis and pericardial effusions
  - Bacterial endocarditis
- Threatened abortion, eclampsia, and preeclampsia
- Unsupervised patients with conditions associated with potential high level of non-compliance
- Spinal puncture and other diagnostic or therapeutic procedures with potential for uncontrollable bleeding
- Hypersensitivity to warfarin or to any other components of this product (e.g., anaphylaxis) [see Adverse Reactions (6)]
- Major regional or lumbar block anesthesia
- Malignant hypertension

5 WARNINGS AND PRECAUTIONS

5.1 Hemorrhage

COUMADIN can cause major or fatal bleeding. Bleeding is more likely to occur within the first month. Risk factors for bleeding include high intensity of anticoagulation (INR >4.0), age greater than or equal to 65, history of highly variable INRs, history of gastrointestinal bleeding, hypertension, cerebrovascular disease, anemia, malignancy, trauma, renal impairment, certain genetic factors [see Clinical Pharmacology (12.5)], certain concomitant drugs [see Drug Interactions (7)], and long duration of warfarin therapy.

Perform regular monitoring of INR in all treated patients. Those at high risk of bleeding may benefit from more frequent INR monitoring, careful dose adjustment to desired INR, and a shortest duration of therapy appropriate for the clinical condition. However, maintenance of INR in the therapeutic range does not eliminate the risk of bleeding.

Drugs, dietary changes, and other factors affect INR levels achieved with COUMADIN therapy. Perform more frequent INR monitoring when starting or stopping other drugs, including botanicals, or when changing dosages of other drugs [see Drug Interactions (7)].

Instruct patients about prevention measures to minimize risk of bleeding and to report signs and symptoms of bleeding [see Patient Counseling Information (17)].

5.2 Tissue Necrosis

Necrosis and/or gangrene of skin and other tissues is an uncommon but serious risk (<0.1%). Necrosis may be associated with local thrombosis and usually appears within a few days of the start of COUMADIN therapy. In severe cases of necrosis, treatment through debridement or amputation of the affected tissue, limb, breast, or penis has been reported.

Careful clinical evaluation is required to determine whether necrosis is caused by an underlying disease. Although various treatments have been attempted, no treatment for necrosis has been considered uniformly effective. Discontinue COUMADIN therapy if necrosis occurs. Consider alternative drugs if continued anticoagulation therapy is necessary.

5.3 Systemic Atheroemboli and Cholesterol Microemboli

Anticoagulation therapy with COUMADIN may enhance the release of atheromatous plaque emboli. Systemic atheroemboli and cholesterol microemboli can present with a variety of signs and symptoms depending on the site of embolization. The most commonly involved visceral organs are the kidneys followed by the pancreas, spleen, and liver. Some cases have progressed to necrosis or death. A distinct syndrome resulting from microemboli to the feet is known as “purple toes syndrome.” Discontinue COUMADIN therapy if such phenomena are observed. Consider alternative drugs if continued anticoagulation therapy is necessary.

5.4 Heparin-Induced Thrombocytopenia

Do not use COUMADIN as initial therapy in patients with heparin-induced thrombocytopenia (HIT) and with heparin-induced thrombocytopenia with thrombosis syndrome (HITTS). Cases of limb ischemia, necrosis, and gangrene have occurred in patients with HIT and HITTS when heparin treatment was discontinued and warfarin therapy was started or continued. In some patients, sequelae have included amputation of the involved area and/or death. Treatment with COUMADIN may be considered after the platelet count has normalized.

5.5 Use in Pregnant Women with Mechanical Heart Valves

COUMADIN can cause fetal harm when administered to a pregnant woman. While COUMADIN is contraindicated during pregnancy, the potential benefits of using COUMADIN may outweigh the risks for pregnant women with mechanical heart valves at high risk of thromboembolism. In those individual situations, the decision to initiate or continue COUMADIN should be reviewed with the patient, taking into consideration the specific risks and benefits pertaining to the individual patient’s medical situation, as well as the most current medical guidelines. COUMADIN exposure during pregnancy causes a recognized pattern of major congenital malformations (warfarin embryopathy and fetotoxicity), fatal fetal hemorrhage, and an increased risk of spontaneous abortion and fetal mortality. If this drug is used during pregnancy, or if the patient becomes pregnant while taking this drug, the patient should be apprised of the potential hazard to a fetus [see Use in Specific Populations (8.1)].

5.6 Females of Reproductive Potential

COUMADIN exposure during pregnancy can cause pregnancy loss, birth defects, or fetal death. Discuss pregnancy planning with females of reproductive potential who are on COUMADIN therapy [see Contraindications (4) and Use in Specific Populations (8.8)].

5.7 Other Clinical Settings with Increased Risks

In the following clinical settings, the risks of COUMADIN therapy may be increased:

- Moderate to severe hepatic impairment
- Infectious diseases or disturbances of intestinal flora (e.g., sprue, antibiotic therapy)
- Use of an indwelling catheter
- Severe to moderate hypertension
- Deficiency in protein C-mediated anticoagulant response: COUMADIN reduces the synthesis of the naturally occurring anticoagulants, protein C and protein S. Hereditary or acquired deficiencies of protein C or its cofactor, protein S, have been associated with tissue necrosis following warfarin administration. Concomitant anticoagulation therapy with heparin for 5 to 7 days during initiation of therapy with COUMADIN may minimize the incidence of tissue necrosis in these patients.
- Eye surgery: In cataract surgery, COUMADIN use was associated with a significant increase in minor complications of sharp needle and local anesthesia block but not associated with potentially sight-threatening operative hemorrhagic complications. As COUMADIN cessation or reduction may lead to serious thromboembolic complications, the decision to discontinue COUMADIN before a relatively less invasive and complex eye surgery, such as lens surgery, should be based upon the risks of anticoagulant therapy weighed against the benefits.
- Polycythemia vera
- Vasculitis
- Diabetes mellitus

5.8 Endogenous Factors Affecting INR

The following factors may be responsible for increased INR response: diarrhea, hepatic disorders, poor nutritional state, steatorrhea, or vitamin K deficiency.

The following factors may be responsible for decreased INR response: increased vitamin K intake or hereditary warfarin resistance.

6 ADVERSE REACTIONS

The following serious adverse reactions to COUMADIN are discussed in greater detail in other sections of the labeling:

- Hemorrhage [see Boxed Warning, Warnings and Precautions (5.1), and Overdosage (10)]
- Necrosis of skin and other tissues [see Warnings and Precautions (5.2)]
- Systemic atheroemboli and cholesterol microemboli [see Warnings and Precautions (5.3)]

Other adverse reactions to COUMADIN include:

- Immune system disorders: hypersensitivity/allergic reactions (including urticaria and anaphylactic reactions)
- Vascular disorders: vasculitis
- Hepatobiliary disorders: hepatitis, elevated liver enzymes. Cholestatic hepatitis has been associated with concomitant administration of COUMADIN and ticlopidine.
- Gastrointestinal disorders: nausea, vomiting, diarrhea, taste perversion, abdominal pain, flatulence, bloating
- Skin disorders: rash, dermatitis (including bullous eruptions), pruritus, alopecia
- Respiratory disorders: tracheal or tracheobronchial calcification
- General disorders: chills

7 DRUG INTERACTIONS

Drugs may interact with COUMADIN through pharmacodynamic or pharmacokinetic mechanisms. Pharmacodynamic mechanisms for drug interactions with COUMADIN are synergism (impaired hemostasis, reduced clotting factor synthesis), competitive antagonism (vitamin K), and alteration of the physiologic control loop for vitamin K metabolism (hereditary resistance). Pharmacokinetic mechanisms for drug interactions with COUMADIN are mainly enzyme induction, enzyme inhibition, and reduced plasma protein binding. It is important to note that some drugs may interact by more than one mechanism.

More frequent INR monitoring should be performed when starting or stopping other drugs, including botanicals, or when changing dosages of other drugs, including drugs intended for short-term use (e.g., antibiotics, antifungals, corticosteroids) [see Boxed Warning].

Consult the labeling of all concurrently used drugs to obtain further information about interactions with COUMADIN or adverse reactions pertaining to bleeding.

7.1 CYP450 Interactions

CYP450 isozymes involved in the metabolism of warfarin include CYP2C9, 2C19, 2C8, 2C18, 1A2, and 3A4. The more potent warfarin S-enantiomer is metabolized by CYP2C9 while the R-enantiomer is metabolized by CYP1A2 and 3A4.

- Inhibitors of CYP2C9, 1A2, and/or 3A4 have the potential to increase the effect (increase INR) of warfarin by increasing the exposure of warfarin.
- Inducers of CYP2C9, 1A2, and/or 3A4 have the potential to decrease the effect (decrease INR) of warfarin by decreasing the exposure of warfarin.

Examples of inhibitors and inducers of CYP2C9, 1A2, and 3A4 are below in Table 2; however, this list should not be considered all-inclusive. Consult the labeling of all concurrently used drugs to obtain further information about CYP450 interaction potential. The CYP450 inhibition and induction potential should be considered when starting, stopping, or changing dose of concomitant mediations. Closely monitor INR if a concomitant drug is a CYP2C9, 1A2, and/or 3A4 inhibitor or inducer.

Table 2: Examples of CYP450 Interactions with Warfarin
Enzyme | Inhibitors | Inducers
CYP2C9 | amiodarone, capecitabine, cotrimoxazole, etravirine, fluconazole, fluvastatin, fluvoxamine, metronidazole, miconazole, oxandrolone, sulfinpyrazone, tigecycline, voriconazole, zafirlukast | aprepitant, bosentan, carbamazepine, phenobarbital, rifampin
CYP1A2 | acyclovir, allopurinol, caffeine, cimetidine, ciprofloxacin, disulfiram, enoxacin, famotidine, fluvoxamine, methoxsalen, mexiletine, norfloxacin, oral contraceptives, phenylpropanolamine, propafenone, propranolol, terbinafine, thiabendazole, ticlopidine, verapamil, zileuton | montelukast, moricizine, omeprazole, phenobarbital, phenytoin, cigarette smoking
CYP3A4 | alprazolam, amiodarone, amlodipine, amprenavir, aprepitant, atorvastatin, atazanavir, bicalutamide, cilostazol, cimetidine, ciprofloxacin, clarithromycin, conivaptan, cyclosporine, darunavir/ritonavir, diltiazem, erythromycin, fluconazole, fluoxetine, fluvoxamine, fosamprenavir, imatinib, indinavir, isoniazid, itraconazole, ketoconazole, lopinavir/ritonavir, nefazodone, nelfinavir, nilotinib, oral contraceptives, posaconazole, ranitidine, ranolazine, ritonavir, saquinavir, telithromycin, tipranavir, voriconazole, zileuton | armodafinil, amprenavir, aprepitant, bosentan, carbamazepine, efavirenz, etravirine, modafinil, nafcillin, phenytoin, pioglitazone, prednisone, rifampin, rufinamide

7.2 Drugs that Increase Bleeding Risk

Examples of drugs known to increase the risk of bleeding are presented in Table 3. Because bleeding risk is increased when these drugs are used concomitantly with warfarin, closely monitor patients receiving any such drug with warfarin.

Table 3: Drugs that Can Increase the Risk of Bleeding
Drug Class | Specific Drugs
Anticoagulants | argatroban, dabigatran, bivalirudin, desirudin, heparin, lepirudin
Antiplatelet Agents | aspirin, cilostazol, clopidogrel, dipyridamole, prasugrel, ticlopidine
Nonsteroidal Anti-Inflammatory Agents | celecoxib, diclofenac, diflunisal, fenoprofen, ibuprofen, indomethacin, ketoprofen, ketorolac, mefenamic acid, naproxen, oxaprozin, piroxicam, sulindac
Serotonin Reuptake Inhibitors | citalopram, desvenlafaxine, duloxetine, escitalopram, fluoxetine, fluvoxamine, milnacipran, paroxetine, sertraline, venlafaxine, vilazodone

7.3 Antibiotics and Antifungals

There have been reports of changes in INR in patients taking warfarin and antibiotics or antifungals, but clinical pharmacokinetic studies have not shown consistent effects of these agents on plasma concentrations of warfarin.

Closely monitor INR when starting or stopping any antibiotic or antifungal in patients taking warfarin.

7.4 Botanical (Herbal) Products and Foods

Exercise caution when botanical (herbal) products are taken concomitantly with COUMADIN. Few adequate, well-controlled studies evaluating the potential for metabolic and/or pharmacologic interactions between botanicals and COUMADIN exist. Due to a lack of manufacturing standardization with botanical medicinal preparations, the amount of active ingredients may vary. This could further confound the ability to assess potential interactions and effects on anticoagulation.

Some botanicals may cause bleeding events when taken alone (e.g., garlic and Ginkgo biloba) and may have anticoagulant, antiplatelet, and/or fibrinolytic properties. These effects would be expected to be additive to the anticoagulant effects of COUMADIN. Conversely, some botanicals may decrease the effects of COUMADIN (e.g., co-enzyme Q10, St. John’s wort, ginseng). Some botanicals and foods can interact with COUMADIN through CYP450 interactions (e.g., echinacea, grapefruit juice, ginkgo, goldenseal, St. John’s wort).

Monitor the patient’s response with additional INR determinations when initiating or discontinuing any botanicals.

8 USE IN SPECIFIC POPULATIONS

8.1 Pregnancy

TERATOGENIC EFFECTS

Pregnancy Category D for women with mechanical heart valves [see Warnings and Precautions (5.5)] and Pregnancy Category X for other pregnant populations [see Contraindications (4)].

COUMADIN is contraindicated in women who are pregnant except in pregnant women with mechanical heart valves, who are at high risk of thromboembolism, and for whom the benefits of COUMADIN may outweigh the risks. COUMADIN can cause fetal harm when administered to a pregnant woman. COUMADIN exposure during pregnancy causes a recognized pattern of major congenital malformations (warfarin embryopathy), fetal hemorrhage, and an increased risk of spontaneous abortion and fetal mortality. The reproductive and developmental effects of COUMADIN have not been evaluated in animals. If this drug is used during pregnancy or if the patient becomes pregnant while taking this drug, the patient should be apprised of the potential hazard to the fetus.

In humans, warfarin crosses the placenta, and concentrations in fetal plasma approach the maternal values. Exposure to warfarin during the first trimester of pregnancy caused a pattern of congenital malformations in about 5% of exposed offspring. Warfarin embryopathy is characterized by nasal hypoplasia with or without stippled epiphyses (chondrodysplasia punctata) and growth retardation (including low birth weight). Central nervous system and eye abnormalities have also been reported, including dorsal midline dysplasia characterized by agenesis of the corpus callosum, Dandy-Walker malformation, midline cerebellar atrophy, and ventral midline dysplasia characterized by optic atrophy. Mental retardation, blindness, schizencephaly, microcephaly, hydrocephalus, and other adverse pregnancy outcomes have been reported following warfarin exposure during the second and third trimesters of pregnancy [see Contraindications (4) and Warnings and Precautions (5.6)].

8.3 Nursing Mothers

Based on published data in 15 nursing mothers, warfarin was not detected in human milk. Among the 15 full-term newborns, 6 nursing infants had documented prothrombin times within the expected range. Prothrombin times were not obtained for the other 9 nursing infants. Monitor breast-feeding infants for bruising or bleeding. Effects in premature infants have not been evaluated. Caution should be exercised when COUMADIN is administered to a nursing woman.

8.4 Pediatric Use

Adequate and well-controlled studies with COUMADIN have not been conducted in any pediatric population, and the optimum dosing, safety, and efficacy in pediatric patients is unknown. Pediatric use of COUMADIN is based on adult data and recommendations, and available limited pediatric data from observational studies and patient registries. Pediatric patients administered COUMADIN should avoid any activity or sport that may result in traumatic injury.

The developing hemostatic system in infants and children results in a changing physiology of thrombosis and response to anticoagulants. Dosing of warfarin in the pediatric population varies by patient age, with infants generally having the highest, and adolescents having the lowest milligram per kilogram dose requirements to maintain target INRs. Because of changing warfarin requirements due to age, concomitant medications, diet, and existing medical condition, target INR ranges may be difficult to achieve and maintain in pediatric patients, and more frequent INR determinations are recommended. Bleeding rates varied by patient population and clinical care center in pediatric observational studies and patient registries.

Infants and children receiving vitamin K-supplemented nutrition, including infant formulas, may be resistant to warfarin therapy, while human milk-fed infants may be sensitive to warfarin therapy.

8.5 Geriatric Use

Of the total number of patients receiving warfarin sodium in controlled clinical trials for which data were available for analysis, 1885 patients (24.4%) were 65 years and older, while 185 patients (2.4%) were 75 years and older. No overall differences in effectiveness or safety were observed between these patients and younger patients, but greater sensitivity of some older individuals cannot be ruled out.

Patients 60 years or older appear to exhibit greater than expected INR response to the anticoagulant effects of warfarin [see Clinical Pharmacology (12.3)]. COUMADIN is contraindicated in any unsupervised patient with senility. Observe caution with administration of COUMADIN to elderly patients in any situation or with any physical condition where added risk of hemorrhage is present. Consider lower initiation and maintenance doses of COUMADIN in elderly patients [see Dosage and Administration (2.2, 2.3)].

8.6 Renal Impairment

Renal clearance is considered to be a minor determinant of anticoagulant response to warfarin. No dosage adjustment is necessary for patients with renal impairment.

8.7 Hepatic Impairment

Hepatic impairment can potentiate the response to warfarin through impaired synthesis of clotting factors and decreased metabolism of warfarin. Use caution when using COUMADIN in these patients.

8.8 Females of Reproductive Potential

COUMADIN exposure during pregnancy can cause spontaneous abortion, birth defects, or fetal death. Females of reproductive potential who are candidates for COUMADIN therapy should be counseled regarding the benefits of therapy and potential reproductive risks. Discuss pregnancy planning with females of reproductive potential who are on COUMADIN therapy. If the patient becomes pregnant while taking COUMADIN, she should be apprised of the potential risks to the fetus.

10 OVERDOSAGE

10.1 Signs and Symptoms

Bleeding (e.g., appearance of blood in stools or urine, hematuria, excessive menstrual bleeding, melena, petechiae, excessive bruising or persistent oozing from superficial injuries, unexplained fall in hemoglobin) is a manifestation of excessive anticoagulation.

10.2 Treatment

The treatment of excessive anticoagulation is based on the level of the INR, the presence or absence of bleeding, and clinical circumstances. Reversal of COUMADIN anticoagulation may be obtained by discontinuing COUMADIN therapy and, if necessary, by administration of oral or parenteral vitamin K1.

The use of vitamin K1 reduces response to subsequent COUMADIN therapy and patients may return to a pretreatment thrombotic status following the rapid reversal of a prolonged INR. Resumption of COUMADIN administration reverses the effect of vitamin K, and a therapeutic INR can again be obtained by careful dosage adjustment. If rapid re-anticoagulation is indicated, heparin may be preferable for initial therapy.

Prothrombin complex concentrate (PCC), fresh frozen plasma, or activated Factor VII treatment may be considered if the requirement to reverse the effects of COUMADIN is urgent. A risk of hepatitis and other viral diseases is associated with the use of blood products; PCC and activated Factor VII are also associated with an increased risk of thrombosis. Therefore, these preparations should be used only in exceptional or life-threatening bleeding episodes secondary to COUMADIN overdosage.

11 DESCRIPTION

COUMADIN (warfarin sodium) is an anticoagulant that acts by inhibiting vitamin K-dependent coagulation factors. Chemically, it is 3-(α-acetonylbenzyl)-4-hydroxycoumarin and is a racemic mixture of the R- and S-enantiomers. Crystalline warfarin sodium is an isopropanol clathrate. Its empirical formula is C19H15NaO4, and its structural formula is represented by the following:

Crystalline warfarin sodium occurs as a white, odorless, crystalline powder that is discolored by light. It is very soluble in water, freely soluble in alcohol, and very slightly soluble in chloroform and ether.

COUMADIN tablets for oral use also contain:

 | All strengths: | Lactose, starch, and magnesium stearate
 | 1 mg: | D&C Red No. 6 Barium Lake
 | 2 mg: | FD&C Blue No. 2 Aluminum Lake and FD&C Red No. 40 Aluminum Lake
 | 2-1/2 mg: | D&C Yellow No. 10 Aluminum Lake and FD&C Blue No. 1 Aluminum Lake
 | 3 mg: | FD&C Yellow No. 6 Aluminum Lake, FD&C Blue No. 2 Aluminum Lake, and FD&C Red No. 40 Aluminum Lake
 | 4 mg: | FD&C Blue No. 1 Aluminum Lake
 | 5 mg: | FD&C Yellow No. 6 Aluminum Lake
 | 6 mg: | FD&C Yellow No. 6 Aluminum Lake and FD&C Blue No. 1 Aluminum Lake
 | 7-1/2 mg: | D&C Yellow No. 10 Aluminum Lake and FD&C Yellow No. 6 Aluminum Lake
 | 10 mg: | Dye-free

COUMADIN for injection for intravenous use is supplied as a sterile, lyophilized powder, which, after reconstitution with 2.7 mL Sterile Water for Injection, contains:

 | Warfarin sodium | 2 mg per mL
 | Sodium phosphate, dibasic, heptahydrate | 4.98 mg per mL
 | Sodium phosphate, monobasic, monohydrate | 0.194 mg per mL
 | Sodium chloride | 0.1 mg per mL
 | Mannitol | 38.0 mg per mL
 | Sodium hydroxide, as needed for pH adjustment to 8.1 to 8.3

12 CLINICAL PHARMACOLOGY

12.1 Mechanism of Action

Warfarin acts by inhibiting the synthesis of vitamin K-dependent clotting factors, which include Factors II, VII, IX, and X, and the anticoagulant proteins C and S. Vitamin K is an essential cofactor for the post ribosomal synthesis of the vitamin K-dependent clotting factors. Vitamin K promotes the biosynthesis of γ-carboxyglutamic acid residues in the proteins that are essential for biological activity. Warfarin is thought to interfere with clotting factor synthesis by inhibition of the C1 subunit of vitamin K epoxide reductase (VKORC1) enzyme complex, thereby reducing the regeneration of vitamin K1 epoxide [see Clinical Pharmacology (12.5)].

12.2 Pharmacodynamics

An anticoagulation effect generally occurs within 24 hours after warfarin administration. However, peak anticoagulant effect may be delayed 72 to 96 hours. The duration of action of a single dose of racemic warfarin is 2 to 5 days. The effects of COUMADIN may become more pronounced as effects of daily maintenance doses overlap. This is consistent with the half-lives of the affected vitamin K-dependent clotting factors and anticoagulation proteins: Factor II - 60 hours, VII - 4 to 6 hours, IX - 24 hours, X - 48 to 72 hours, and proteins C and S are approximately 8 hours and 30 hours, respectively.

12.3 Pharmacokinetics

COUMADIN is a racemic mixture of the R- and S-enantiomers of warfarin. The S-enantiomer exhibits 2 to 5 times more anticoagulant activity than the R-enantiomer in humans, but generally has a more rapid clearance.

Absorption

Warfarin is essentially completely absorbed after oral administration, with peak concentration generally attained within the first 4 hours.

Distribution

Warfarin distributes into a relatively small apparent volume of distribution of about 0.14 L/kg. A distribution phase lasting 6 to 12 hours is distinguishable after rapid intravenous or oral administration of an aqueous solution. Approximately 99% of the drug is bound to plasma proteins.

Metabolism

The elimination of warfarin is almost entirely by metabolism. Warfarin is stereoselectively metabolized by hepatic cytochrome P-450 (CYP450) microsomal enzymes to inactive hydroxylated metabolites (predominant route) and by reductases to reduced metabolites (warfarin alcohols) with minimal anticoagulant activity. Identified metabolites of warfarin include dehydrowarfarin, two diastereoisomer alcohols, and 4′-, 6-, 7-, 8-, and 10-hydroxywarfarin. The CYP450 isozymes involved in the metabolism of warfarin include CYP2C9, 2C19, 2C8, 2C18, 1A2, and 3A4. CYP2C9, a polymorphic enzyme, is likely to be the principal form of human liver CYP450 that modulates the in vivo anticoagulant activity of warfarin. Patients with one or more variant CYP2C9 alleles have decreased S-warfarin clearance [see Clinical Pharmacology (12.5)].

Excretion

The terminal half-life of warfarin after a single dose is approximately 1 week; however, the effective half-life ranges from 20 to 60 hours, with a mean of about 40 hours. The clearance of R-warfarin is generally half that of S-warfarin, thus as the volumes of distribution are similar, the half-life of R-warfarin is longer than that of S-warfarin. The half-life of R-warfarin ranges from 37 to 89 hours, while that of S-warfarin ranges from 21 to 43 hours. Studies with radiolabeled drug have demonstrated that up to 92% of the orally administered dose is recovered in urine. Very little warfarin is excreted unchanged in urine. Urinary excretion is in the form of metabolites.

Geriatric Patients

Patients 60 years or older appear to exhibit greater than expected INR response to the anticoagulant effects of warfarin. The cause of the increased sensitivity to the anticoagulant effects of warfarin in this age group is unknown but may be due to a combination of pharmacokinetic and pharmacodynamic factors. Limited information suggests there is no difference in the clearance of S-warfarin; however, there may be a slight decrease in the clearance of R-warfarin in the elderly as compared to the young. Therefore, as patient age increases, a lower dose of warfarin is usually required to produce a therapeutic level of anticoagulation [see Dosage and Administration (2.3, 2.4)].

Asian Patients

Asian patients may require lower initiation and maintenance doses of warfarin. A non-controlled study of 151 Chinese outpatients stabilized on warfarin for various indications reported a mean daily warfarin requirement of 3.3 ± 1.4 mg to achieve an INR of 2 to 2.5. Patient age was the most important determinant of warfarin requirement in these patients, with a progressively lower warfarin requirement with increasing age.

12.5 Pharmacogenomics

CYP2C9 and VKORC1 Polymorphisms

The S-enantiomer of warfarin is mainly metabolized to 7-hydroxywarfarin by CYP2C9, a polymorphic enzyme. The variant alleles, CYP2C9*2 and CYP2C9*3, result in decreased in vitro CYP2C9 enzymatic 7-hydroxylation of S-warfarin. The frequencies of these alleles in Caucasians are approximately 11% and 7% for CYP2C9*2 and CYP2C9*3, respectively.

Other CYP2C9 alleles associated with reduced enzymatic activity occur at lower frequencies, including *5, *6, and *11 alleles in populations of African ancestry and *5, *9, and *11 alleles in Caucasians.

Warfarin reduces the regeneration of vitamin K from vitamin K epoxide in the vitamin K cycle through inhibition of VKOR, a multiprotein enzyme complex. Certain single nucleotide polymorphisms in the VKORC1 gene (e.g., –1639G>A) have been associated with variable warfarin dose requirements. VKORC1 and CYP2C9 gene variants generally explain the largest proportion of known variability in warfarin dose requirements.

CYP2C9 and VKORC1 genotype information, when available, can assist in selection of the initial dose of warfarin [see Dosage and Administration (2.3)].

13 NONCLINICAL TOXICOLOGY

13.1 Carcinogenesis, Mutagenesis, Impairment of Fertility

Carcinogenicity, mutagenicity, or fertility studies have not been performed with warfarin.

14 CLINICAL STUDIES

14.1 Atrial Fibrillation

In five prospective, randomized, controlled clinical trials involving 3711 patients with non-rheumatic AF, warfarin significantly reduced the risk of systemic thromboembolism including stroke (see Table 4). The risk reduction ranged from 60% to 86% in all except one trial (CAFA: 45%), which was stopped early due to published positive results from two of these trials. The incidence of major bleeding in these trials ranged from 0.6% to 2.7% (see Table 4).

Table 4: Clinical Studies of Warfarin in Non-Rheumatic AF Patients*
 | N |  |  |  | Thromboembolism |  | % Major Bleeding
Study | Warfarin- Treated Patients | Control Patients | PT Ratio | INR | % Risk Reduction | p-value | Warfarin- Treated Patients | Control Patients
AFASAK | 335 | 336 | 1.5-2.0 | 2.8-4.2 | 60 | 0.027 | 0.6 | 0.0
SPAF | 210 | 211 | 1.3-1.8 | 2.0-4.5 | 67 | 0.01 | 1.9 | 1.9
BAATAF | 212 | 208 | 1.2-1.5 | 1.5-2.7 | 86 | <0.05 | 0.9 | 0.5
CAFA | 187 | 191 | 1.3-1.6 | 2.0-3.0 | 45 | 0.25 | 2.7 | 0.5
SPINAF | 260 | 265 | 1.2-1.5 | 1.4-2.8 | 79 | 0.001 | 2.3 | 1.5
*All study results of warfarin vs. control are based on intention-to-treat analysis and include ischemic stroke and systemic thromboembolism, excluding hemorrhagic stroke and transient ischemic attacks.

Trials in patients with both AF and mitral stenosis suggest a benefit from anticoagulation with COUMADIN [see Dosage and Administration (2.2)].

14.2 Mechanical and Bioprosthetic Heart Valves

In a prospective, randomized, open-label, positive-controlled study in 254 patients with mechanical prosthetic heart valves, the thromboembolic-free interval was found to be significantly greater in patients treated with warfarin alone compared with dipyridamole/aspirin-treated patients (p<0.005) and pentoxifylline/aspirin-treated patients (p<0.05). The results of this study are presented in Table 5.

Table 5: Prospective, Randomized, Open-Label, Positive-Controlled Clinical Study of Warfarin in Patients with Mechanical Prosthetic Heart Valves
 | Patients Treated With
 | Warfarin | Dipyridamole/Aspirin | Pentoxifylline/Aspirin
Event
Thromboembolism | 2.2/100 py | 8.6/100 py | 7.9/100 py
Major Bleeding | 2.5/100 py | 0.0/100 py | 0.9/100 py
py=patient years

In a prospective, open-label, clinical study comparing moderate (INR 2.65) vs. high intensity (INR 9.0) warfarin therapies in 258 patients with mechanical prosthetic heart valves, thromboembolism occurred with similar frequency in the two groups (4.0 and 3.7 events per 100 patient years, respectively). Major bleeding was more common in the high intensity group. The results of this study are presented in Table 6.

Table 6: Prospective, Open-Label Clinical Study of Warfarin in Patients with Mechanical Prosthetic Heart Valves
Event | Moderate Warfarin Therapy INR 2.65 | High Intensity Warfarin Therapy INR 9.0
Thromboembolism | 4.0/100 py | 3.7/100 py
Major Bleeding | 0.95/100 py | 2.1/100 py
py=patient years

In a randomized trial in 210 patients comparing two intensities of warfarin therapy (INR 2.0-2.25 vs. INR 2.5-4.0) for a three-month period following tissue heart valve replacement, thromboembolism occurred with similar frequency in the two groups (major embolic events 2.0% vs. 1.9%, respectively, and minor embolic events 10.8% vs. 10.2%, respectively). Major hemorrhages occurred in 4.6% of patients in the higher intensity INR group compared to zero in the lower intensity INR group.

14.3 Myocardial Infarction

WARIS (The Warfarin Re-Infarction Study) was a double-blind, randomized study of 1214 patients 2 to 4 weeks post-infarction treated with warfarin to a target INR of 2.8 to 4.8. The primary endpoint was a composite of total mortality and recurrent infarction. A secondary endpoint of cerebrovascular events was assessed. Mean follow-up of the patients was 37 months. The results for each endpoint separately, including an analysis of vascular death, are provided in Table 7.

Table 7: WARIS – Endpoint Analysis of Separate Events
Event | Warfarin (N=607) | Placebo (N=607) | RR (95% CI) | % Risk Reduction (p-value)
Total Patient Years of Follow-up | 2018 | 1944
Total Mortality | 94 (4.7/100 py) | 123 (6.3/100 py) | 0.76 (0.60, 0.97) | 24 (p=0.030)
Vascular Death | 82 (4.1/100 py) | 105 (5.4/100 py) | 0.78 (0.60, 1.02) | 22 (p=0.068)
Recurrent MI | 82 (4.1/100 py) | 124 (6.4/100 py) | 0.66 (0.51, 0.85) | 34 (p=0.001)
Cerebrovascular Event | 20 (1.0/100 py) | 44 (2.3/100 py) | 0.46 (0.28, 0.75) | 54 (p=0.002)
RR=Relative risk; Risk reduction=(1 - RR); CI=Confidence interval; MI=Myocardial infarction; py=patient years

WARIS II (The Warfarin, Aspirin, Re-Infarction Study) was an open-label, randomized study of 3630 patients hospitalized for acute myocardial infarction treated with warfarin to a target INR 2.8 to 4.2, aspirin 160 mg per day, or warfarin to a target INR 2.0 to 2.5 plus aspirin 75 mg per day prior to hospital discharge. The primary endpoint was a composite of death, nonfatal reinfarction, or thromboembolic stroke. The mean duration of observation was approximately 4 years. The results for WARIS II are provided in Table 8.

Table 8: WARIS II - Distribution of Events According to Treatment Group
Event | Aspirin (N=1206) | Warfarin (N=1216) | Aspirin plus Warfarin (N=1208) | Rate Ratio (95% CI) | p-value
 | No. of Events
Major Bleedinga | 8 | 33 | 28 | 3.35b (ND) 4.00c (ND) | ND ND
Minor Bleedingd | 39 | 103 | 133 | 3.21b (ND) 2.55c (ND) | ND ND
Composite Endpointse | 241 | 203 | 181 | 0.81 (0.69-0.95)b 0.71 (0.60-0.83)c | 0.03 0.001
Reinfarction | 117 | 90 | 69 | 0.56 (0.41-0.78)b 0.74 (0.55-0.98)c | <0.001 0.03
Thromboembolic Stroke | 32 | 17 | 17 | 0.52 (0.28-0.98)b 0.52 (0.28-0.97)c | 0.03 0.03
Death | 92 | 96 | 95 |  | 0.82
a Major bleeding episodes were defined as nonfatal cerebral hemorrhage or bleeding necessitating surgical intervention or blood transfusion.
b The rate ratio is for aspirin plus warfarin as compared with aspirin.
c The rate ratio is for warfarin as compared with aspirin.
d Minor bleeding episodes were defined as non-cerebral hemorrhage not necessitating surgical intervention or blood transfusion.
e Includes death, nonfatal reinfarction, and thromboembolic cerebral stroke.
CI=confidence interval
ND=not determined

There were approximately four times as many major bleeding episodes in the two groups receiving warfarin than in the group receiving aspirin alone. Major bleeding episodes were not more frequent among patients receiving aspirin plus warfarin than among those receiving warfarin alone, but the incidence of minor bleeding episodes was higher in the combined therapy group.

15 REFERENCES

- Ansell J, Hirsh J, Hylek E, Jacobson A, Crowther M, Palareti G. Pharmacology and management of the vitamin K antagonists. American College of Chest Physicians Evidence-Based Clinical Practice Guidelines. 8th Ed. Chest. 2008;133:160S-198S.
- Kearon C, Kahn SR, Agnelli G, Goldhaber S, Raskob GE, Comerota AJ. Antithrombotic therapy for venous thromboembolic disease. American College of Chest Physicians Evidence-Based Clinical Practice Guidelines. 8th Ed. Chest. 2008;133:454S-545S.
- Singer DE, Albers GW, Dalen JE, et al. Antithrombotic therapy in atrial fibrillation. American College of Chest Physicians Evidence-Based Clinical Practice Guidelines. 8th Ed. Chest. 2008;133:546S-592S.
- Becker RC, Meade TW, Berger PB, et al. The primary and secondary prevention of coronary artery disease. American College of Chest Physicians Evidence-Based Clinical Practice Guidelines. 8th Ed. Chest. 2008;133:776S-814S.
- Salem DN, O'Gara PT, Madias C, Pauker SG. Valvular and structural heart disease. American College of Chest Physicians Evidence-Based Clinical Practice Guidelines. 8th Ed. Chest. 2008;133:593S-629S.
- Monagle P, Chalmers E, Chan A, et al. Antithrombotic therapy in neonates and children. American College of Chest Physicians Evidence-Based Clinical Practice Guidelines. 8th Ed. Chest. 2008;133:887S-968S.

16 HOW SUPPLIED/STORAGE AND HANDLING

COUMADIN tablets are single-scored, with one face imprinted numerically with 1, 4, 5, 6, 7-1/2 superimposed and inscribed with with “COUMADIN” and with the opposite face plain. COUMADIN is available with potencies and colors as follows:

1 mg pink | bottles of 10 NDC 54868-2128-0 bottles of 30 NDC 54868-2128-2 bottles of 90 NDC 54868-2128-3
4 mg blue | bottles of 10 NDC 54868-3399-2 bottles of 30 NDC 54868-3399-1 bottles of 100 NDC 54868-3399-0
5 mg peach | bottles of 10 NDC 54868-1259-6 bottles of 20 NDC 54868-1259-0 bottles of 30 NDC 54868-1259-1 bottles of 75 NDC 54868-1256-7 bottles of 90 NDC 54868-1259-5
6 mg teal | bottles of 10 NDC 54868-5255-1 bottles of 30 NDC 54868-5255-0
7-1.2 mg yellow | bottles of 30 NDC 54868-2252-1

Protect from light. Store at controlled room temperature (59°-86°F, 15°-30°C). Dispense in a tight, light-resistant container as defined in the USP.

17 PATIENT COUNSELING INFORMATION

See FDA-approved patient labeling (Medication Guide).

Advise patients to:

- Tell their physician if they fall often as this may increase their risk for complications.
- Strictly adhere to the prescribed dosage schedule. Do not take or discontinue any other drug, including salicylates (e.g., aspirin and topical analgesics), other over-the-counter drugs, and botanical (herbal) products except on advice of your physician.
- Notify their physician immediately if any unusual bleeding or symptoms occur. Signs and symptoms of bleeding include: pain, swelling or discomfort, prolonged bleeding from cuts, increased menstrual flow or vaginal bleeding, nosebleeds, bleeding of gums from brushing, unusual bleeding or bruising, red or dark brown urine, red or tar black stools, headache, dizziness, or weakness.
- Contact their doctor
  - immediately if they think they are pregnant
  - to discuss pregnancy planning
  - if they are considering breast-feeding
- Avoid any activity or sport that may result in traumatic injury.
- Obtain prothrombin time tests and make regular visits to their physician or clinic to monitor therapy.
- Carry identification stating that they are taking COUMADIN.
- If the prescribed dose of COUMADIN is missed, take the dose as soon as possible on the same day but do not take a double dose of COUMADIN the next day to make up for missed doses.
- Eat a normal, balanced diet to maintain a consistent intake of vitamin K. Avoid drastic changes in dietary habits, such as eating large amounts of leafy, green vegetables.
- Contact their physician to report any serious illness, such as severe diarrhea, infection, or fever.
- Be aware that if therapy with COUMADIN is discontinued, the anticoagulant effects of COUMADIN may persist for about 2 to 5 days.

Distributed by:
Bristol-Myers Squibb Company
Princeton, New Jersey 08543 USA

COUMADIN® is a trademark of Bristol-Myers Squibb Pharma Company.

Copyright © Bristol-Myers Squibb Company 2011

Printed in USA
1274054A0 / 1274029A0 / 1274055A0 / 1274053A0
Rev October 2011

MEDICATION GUIDE

COUMADIN® (COU-ma-din)
(warfarin sodium)

Read this Medication Guide before you start taking COUMADIN (warfarin sodium) and each time you get a refill. There may be new information. This Medication Guide does not take the place of talking to your healthcare provider about your medical condition or treatment. You and your healthcare provider should talk about COUMADIN when you start taking it and at regular checkups.

What is the most important information I should know about COUMADIN?

COUMADIN can cause bleeding which can be serious and sometimes lead to death. This is because COUMADIN is a blood thinner medicine that lowers the chance of blood clots forming in your body.

- You may have a higher risk of bleeding if you take COUMADIN and:
  - are 65 years of age or older
  - have a history of stomach or intestinal bleeding
  - have high blood pressure (hypertension)
  - have a history of stroke, or "mini-stroke" (transient ischemic attack or TIA)
  - have serious heart disease
  - have a low blood count or cancer
  - have had trauma, such as an accident or surgery
  - have kidney problems
  - take other medicines that increase your risk of bleeding, including:
    - a medicine that contains heparin
    - other medicines to prevent or treat blood clots
    - nonsteroidal anti-inflammatory drugs (NSAIDs)
  - take warfarin sodium for a long time. Warfarin sodium is the active ingredient in COUMADIN.

Tell your healthcare provider if you take any of these medicines. Ask your healthcare provider if you are not sure if your medicine is one listed above.

Many other medicines can interact with COUMADIN and affect the dose you need or increase COUMADIN side effects. Do not change or stop any of your medicines or start any new medicines before you talk to your healthcare provider.

Do not take other medicines that contain warfarin sodium while taking COUMADIN.

- Get your regular blood test to check for your response to COUMADIN. This blood test is called an INR test. The INR test checks to see how fast your blood clots. Your healthcare provider will decide what INR numbers are best for you. Your dose of COUMADIN will be adjusted to keep your INR in a target range for you.
- Call your healthcare provider right away if you get any of the following signs or symptoms of bleeding problems:
  - pain, swelling, or discomfort
  - headaches, dizziness, or weakness
  - unusual bruising (bruises that develop without known cause or grow in size)
  - nosebleeds
  - bleeding gums
  - bleeding from cuts takes a long time to stop
  - menstrual bleeding or vaginal bleeding that is heavier than normal
  - pink or brown urine
  - red or black stools
  - coughing up blood
  - vomiting blood or material that looks like coffee grounds
- Some foods and beverages can interact with COUMADIN and affect your treatment and dose.
  - Eat a normal, balanced diet. Talk to your healthcare provider before you make any diet changes. Do not eat large amounts of leafy, green vegetables. Leafy, green vegetables contain vitamin K. Certain vegetable oils also contain large amounts of vitamin K. Too much vitamin K can lower the effect of COUMADIN.
- Always tell all of your healthcare providers that you take COUMADIN.
- Wear or carry information that you take COUMADIN.

See "What are the possible side effects of COUMADIN?" for more information about side effects.

What is COUMADIN?

COUMADIN is prescription medicine used to treat blood clots and to lower the chance of blood clots forming in your body. Blood clots can cause a stroke, heart attack, or other serious conditions if they form in the legs or lungs.

It is not known if COUMADIN is safe and effective in children.

Who should not take COUMADIN?

Do not take COUMADIN if:

- your chance of having bleeding problems is higher than the possible benefit of treatment. Your healthcare provider will decide if COUMADIN is right for you. Talk to your healthcare provider about all of your health conditions.
- you are pregnant unless you have a mechanical heart valve. COUMADIN may cause birth defects, miscarriage, or death of your unborn baby.
- you are allergic to warfarin or any of the other ingredients in COUMADIN. See the end of this leaflet for a complete list of ingredients in COUMADIN.

What should I tell my healthcare provider before taking COUMADIN?

Before you take COUMADIN, tell your healthcare provider if you:

- have bleeding problems
- fall often
- have liver or kidney problems
- have high blood pressure
- have a heart problem called congestive heart failure
- have diabetes
- plan to have any surgery or a dental procedure
- have any other medical conditions
- are pregnant or plan to become pregnant. See "Who should not take COUMADIN?"
- are breast-feeding. You and your healthcare provider should decide if you will take COUMADIN and breast-feed.

Tell all of your healthcare providers and dentists that you are taking COUMADIN. They should talk to the healthcare provider who prescribed COUMADIN for you before you have any surgery or dental procedure. Your COUMADIN may need to be stopped for a short time or you may need your dose adjusted.

Tell your healthcare provider about all the medicines you take, including prescription and non-prescription medicines, vitamins, and herbal supplements. Some of your other medicines may affect the way COUMADIN works. Certain medicines may increase your risk of bleeding. See "What is the most important information I should know about COUMADIN?"

Know the medicines you take. Keep a list of them to show your healthcare provider and pharmacist when you get a new medicine.

How should I take COUMADIN?

- Take COUMADIN exactly as prescribed. Your healthcare provider will adjust your dose from time to time depending on your response to COUMADIN.
- You must have regular blood tests and visits with your healthcare provider to monitor your condition.
- If you miss a dose of COUMADIN, call your healthcare provider. Take the dose as soon as possible on the same day. Do not take a double dose of COUMADIN the next day to make up for a missed dose.
- Call your healthcare provider right away if you:
  - take too much COUMADIN
  - are sick with diarrhea, an infection, or have a fever
  - fall or injure yourself, especially if you hit your head. Your healthcare provider may need to check you

What should I avoid while taking COUMADIN?

- Do not do any activity or sport that may cause a serious injury.

What are the possible side effects of COUMADIN?

COUMADIN may cause serious side effects including:

- See "What is the most important information I should know about COUMADIN?"
  - Death of skin tissue (skin necrosis or gangrene). This can happen soon after starting COUMADIN. It happens because blood clots form and block blood flow to an area of your body. Call your healthcare provider right away if you have pain, color, or temperature change to any area of your body. You may need medical care right away to prevent death or loss (amputation) of your affected body part.
  - "Purple toes syndrome." Call your healthcare provider right away if you have pain in your toes and they look purple in color or dark in color.

Tell your healthcare provider if you have any side effect that bothers you or does not go away.

These are not all of the side effects of COUMADIN. For more information, ask your healthcare provider or pharmacist.

Call your doctor for medical advice about side effects. You may report side effects to FDA at 1-800-FDA-1088.

How should I store COUMADIN?

- Store COUMADIN at 59°F to 86°F (15°C to 30°C).
- Keep COUMADIN in a tightly closed container, and keep COUMADIN out of the light.

Keep COUMADIN and all medicines out of the reach of children.

General Information about COUMADIN.

Medicines are sometimes prescribed for purposes other than those listed in a Medication Guide. Do not use COUMADIN for a condition for which it was not prescribed. Do not give COUMADIN to other people, even if they have the same symptoms that you have. It may harm them.

This Medication Guide summarizes the most important information about COUMADIN. If you would like more information, talk with your healthcare provider. You can ask your healthcare provider or pharmacist for information about COUMADIN that is written for healthcare professionals.

If you would like more information, go to www.coumadin.com or call 1-800-321-1335.

What are the ingredients in COUMADIN?

Active ingredient: Warfarin Sodium

Inactive ingredients: Lactose, starch, and magnesium stearate. The following tablets contain:

 | 1 mg: | D&C Red No. 6 Barium Lake
 | 2 mg: | FD&C Blue No. 2 Aluminum Lake and FD&C Red No. 40 Aluminum Lake
 | 2-1/2 mg: | D&C Yellow No. 10 Aluminum Lake and FD&C Blue No. 1 Aluminum Lake
 | 3 mg: | FD&C Yellow No. 6 Aluminum Lake, FD&C Blue No. 2 Aluminum Lake, and FD&C Red No. 40 Aluminum Lake
 | 4 mg: | FD&C Blue No. 1 Aluminum Lake
 | 5 mg: | FD&C Yellow No. 6 Aluminum Lake
 | 6 mg: | FD&C Yellow No. 6 Aluminum Lake and FD&C Blue No. 1 Aluminum Lake
 | 7-1/2 mg: | D&C Yellow No. 10 Aluminum Lake and FD&C Yellow No. 6 Aluminum Lake

This Medication Guide has been approved by the U.S. Food and Drug Administration.

COUMADIN is distributed by:
Bristol-Myers Squibb Company
Princeton, New Jersey 08543 USA

COUMADIN® is a registered trademark of Bristol-Myers Squibb Pharma Company.

**The brands listed (other than COUMADIN®) are registered trademarks of their respective owners and are not trademarks of Bristol-Myers Squibb Company.

1258498A3 / 1215385A4 / 1205734A4 / 1205736A4
Rev October 2011

PACKAGE LABEL

-------------------------------------------------------
REPRESENTATIVE PACKAGING

See How Supplied section for a complete list of available packages of COUMADIN.

1 mg Rx only
COUMADIN®
(Warfarin Sodium Tablets, USP)
Crystalline*
DISPENSE WITH MEDICATION GUIDE
HIGHLY POTENT ANTICOAGULANT
WARNING: Serious bleeding results from overdosage. Do not use or dispense before reading directions and warnings in accompanying product information.
DOSAGE: See package insert.

PACKAGE LABEL

4 mg Rx only
COUMADIN®
(Warfarin Sodium Tablets, USP)
Crystalline*
DISPENSE WITH MEDICATION GUIDE
HIGHLY POTENT ANTICOAGULANT
WARNING: Serious bleeding results from overdosage. Do not use or dispense before reading directions and warnings in accompanying product information.
DOSAGE: See package insert.

PACKAGE LABEL

5 mg Rx only
COUMADIN®
(Warfarin Sodium Tablets, USP)
Crystalline*
DISPENSE WITH MEDICATION GUIDE
HIGHLY POTENT ANTICOAGULANT
WARNING: Serious bleeding results from overdosage. Do not use or dispense before reading directions and warnings in accompanying product information.
DOSAGE: See package insert.

PACKAGE LABEL

6 mg Rx only
COUMADIN®
(Warfarin Sodium Tablets, USP)
Crystalline*
DISPENSE WITH MEDICATION GUIDE
HIGHLY POTENT ANTICOAGULANT
WARNING: Serious bleeding results from overdosage. Do not use or dispense before reading directions and warnings in accompanying product information.
DOSAGE: See package insert.

PACKAGE LABEL

7½ mg Rx only
COUMADIN®
(Warfarin Sodium Tablets, USP)
Crystalline*
DISPENSE WITH MEDICATION GUIDE
HIGHLY POTENT ANTICOAGULANT
WARNING: Serious bleeding results from overdosage. Do not use or dispense before reading directions and warnings in accompanying product information.
DOSAGE: See package insert.